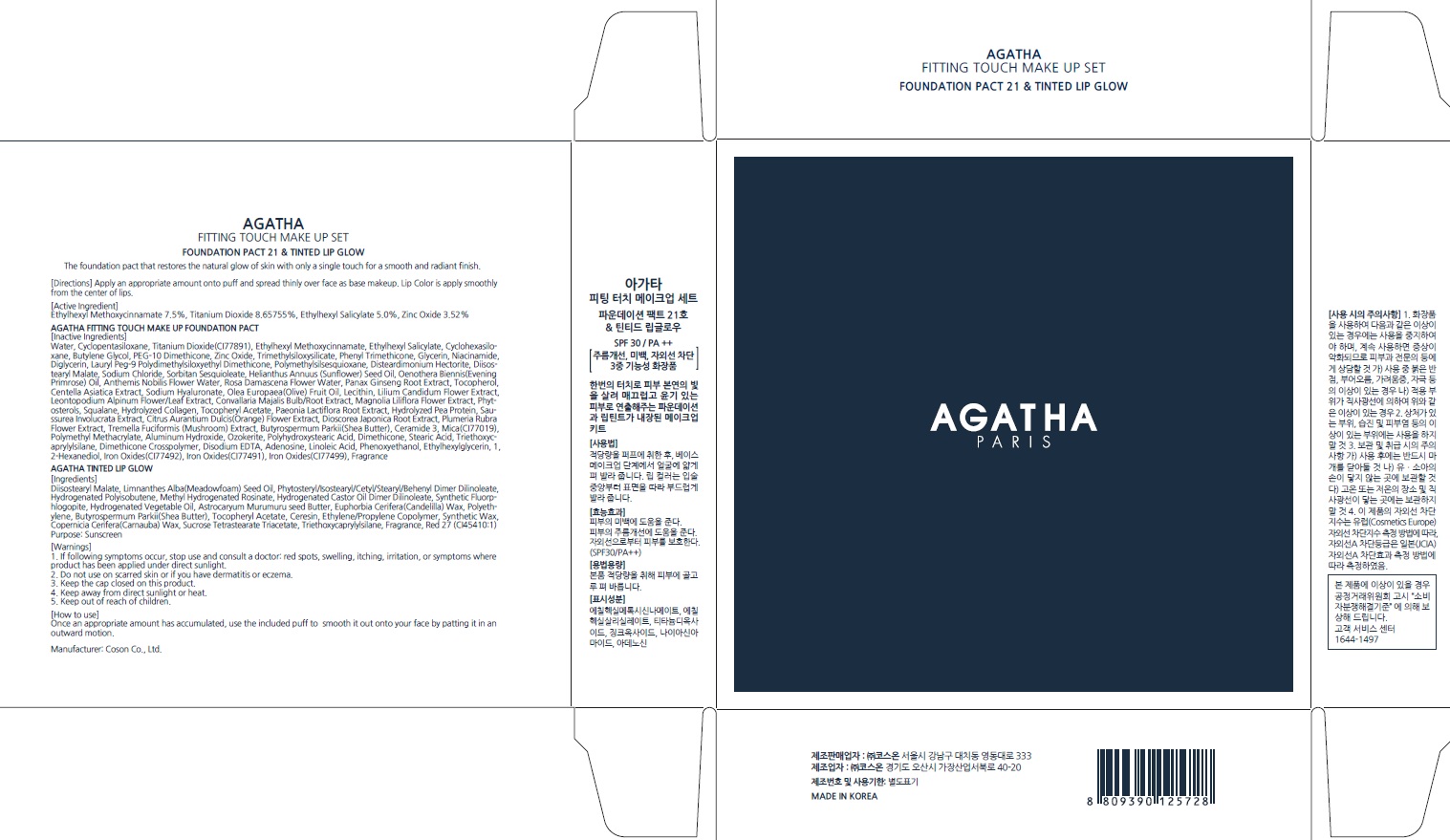 DRUG LABEL: AGATHA FITTING TOUCH MAKE UP SET
NDC: 62171-070 | Form: POWDER
Manufacturer: Coson Co., Ltd.
Category: otc | Type: HUMAN OTC DRUG LABEL
Date: 20160113

ACTIVE INGREDIENTS: Octinoxate 0.67 g/9 g; Titanium Dioxide 0.77 g/9 g; Octisalate 0.45 g/9 g; Zinc Oxide 0.31 g/9 g
INACTIVE INGREDIENTS: Water; Butylene Glycol

ACTIVE INGREDIENT

Active Ingredient: Ethylhexyl Methoxycinnamate 7.5%, Titanium Dioxide 8.65755%, Ethylhexyl Salicylate 5.0%, Zinc Oxide 3.52%

INACTIVE INGREDIENT

AGATHA FITTING TOUCH MAKE UP FOUNDATION PACT - Inactive Ingredients: Water, Cyclopentasiloxane, Cyclohexasiloxane, Butylene Glycol, PEG-10 Dimethicone, Trimethylsiloxysilicate, Phenyl Trimethicone, Glycerin, Niacinamide, Diglycerin, Lauryl Peg-9 Polydimethylsiloxyethyl Dimethicone, Polymethylsilsesquioxane, Disteardimonium Hectorite, Diisostearyl Malate, Sodium Chloride, Sorbitan Sesquioleate, Helianthus Annuus (Sunflower) Seed Oil, Oenothera Biennis(Evening Primrose) Oil, Anthemis Nobilis Flower Water, Rosa Damascena Flower Water, Panax Ginseng Root Extract, Tocopherol, Centella Asiatica Extract, Sodium Hyaluronate, Olea Europaea(Olive) Fruit Oil, Lecithin, Lilium Candidum Flower Extract, Leontopodium Alpinum Flower/Leaf Extract, Convallaria Majalis Bulb/Root Extract, Magnolia Liliflora Flower Extract, Phytosterols, Squalane, Hydrolyzed Collagen, Tocopheryl Acetate, Paeonia Lactiflora Root Extract, Hydrolyzed Pea Protein, Saussurea Involucrata Extract, Citrus Aurantium Dulcis(Orange) Flower Extract, Dioscorea Japonica Root Extract, Plumeria Rubra Flower Extract, Tremella Fuciformis (Mushroom) Extract, Butyrospermum Parkii(Shea Butter), Ceramide 3, Mica(CI77019), Polymethyl Methacrylate, Aluminum Hydroxide, Ozokerite, Polyhydroxystearic Acid, Dimethicone, Stearic Acid, Triethoxycaprylylsilane, Dimethicone Crosspolymer, Disodium EDTA, Adenosine, Linoleic Acid, Phenoxyethanol, Ethylhexylglycerin, 1,2-Hexanediol, Iron Oxides(CI77492), Iron Oxides(CI77491), Iron Oxides(CI77499), Fragrance

AGATHA TINTED LIP GLOW - Ingredients: Diisostearyl Malate, Limnanthes Alba(Meadowfoam) Seed Oil, Phytosteryl/Isostearyl/Cetyl/Stearyl/Behenyl Dimer Dilinoleate, Hydrogenated Polyisobutene, Methyl Hydrogenated Rosinate, Hydrogenated Castor Oil Dimer Dilinoleate, Synthetic Fluorphlogopite, Hydrogenated Vegetable Oil, Astrocaryum Murumuru seed Butter, Euphorbia Cerifera(Candelilla) Wax, Polyethylene, Butyrospermum Parkii(Shea Butter), Tocopheryl Acetate, Ceresin, Ethylene/Propylene Copolymer, Synthetic Wax, Copernicia Cerifera(Carnauba) Wax, Sucrose Tetrastearate Triacetate, Triethoxycaprylylsilane, Fragrance, Red 27 (CI45410:1)

PURPOSE

Purpose: Sunscreen

WARNINGS

Warnings: 1. If following symptoms occur, stop use and consult a doctor: red spots, swelling, itching, irritation, or symptoms where product has been applied under direct sunlight. 2. Do not use on scarred skin or if you have dermatitis or eczema. 3. Keep the cap closed on this product. 4. Keep away from direct sunlight or heat. 5. Keep out of reach of children.

How to use: Once an appropriate amount has accumulated, use the included puff to smooth it out onto your face by patting it in an outward motion.